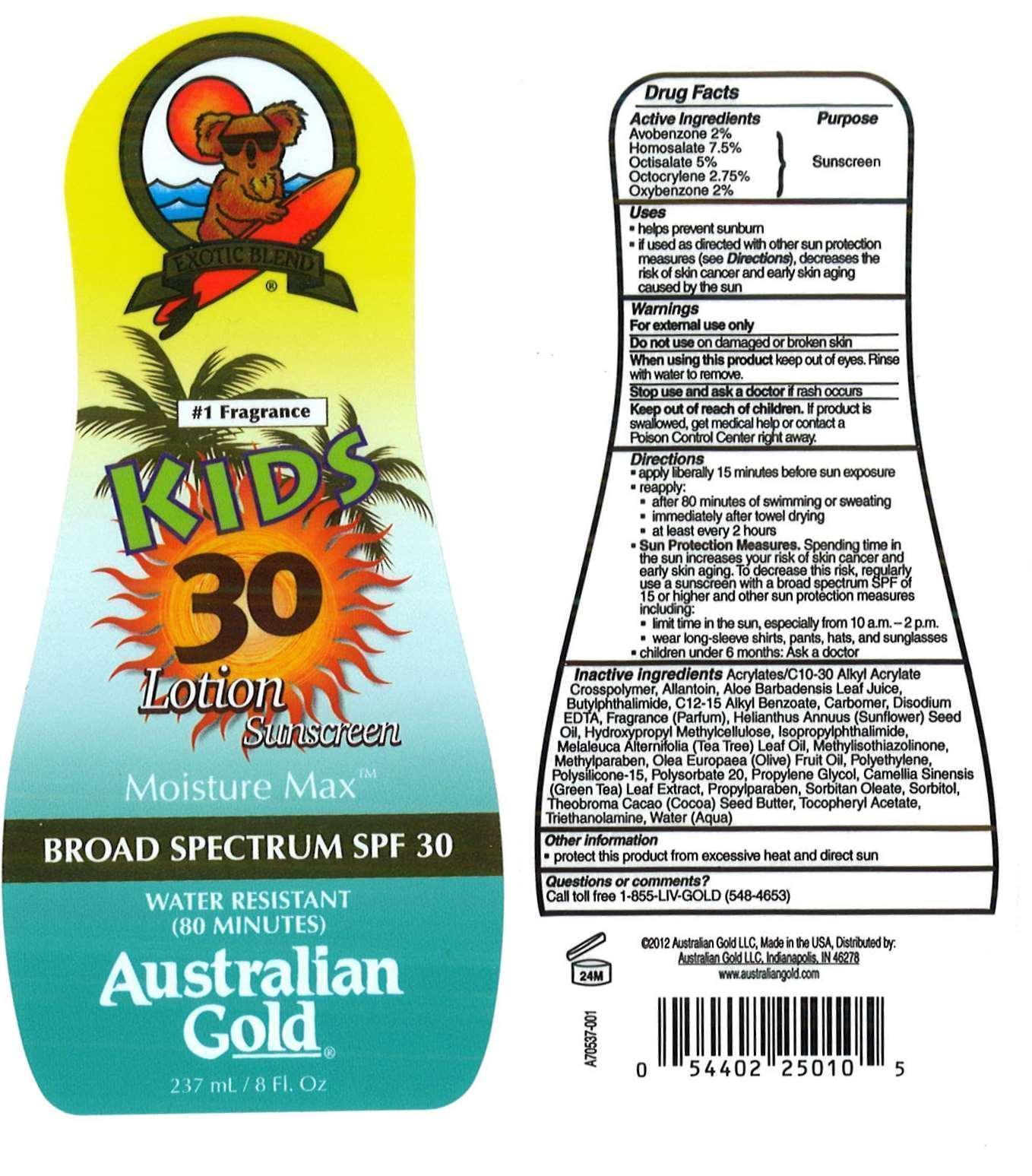 DRUG LABEL: Australian Gold
NDC: 58443-0017 | Form: LOTION
Manufacturer: Prime Enterprises, Inc.
Category: otc | Type: HUMAN OTC DRUG LABEL
Date: 20200117

ACTIVE INGREDIENTS: AVOBENZONE 20 mg/1 mL; HOMOSALATE 75.1 mg/1 mL; OCTISALATE 50.1 mg/1 mL; OCTOCRYLENE 27.5 mg/1 mL; OXYBENZONE 20 mg/1 mL
INACTIVE INGREDIENTS: CARBOMER COPOLYMER TYPE A; ALLANTOIN; ALOE VERA LEAF; 3-BUTYLPHTHALIDE; ISOPROPYLPHTHALIMIDE; ALKYL (C12-15) BENZOATE; CARBOMER HOMOPOLYMER TYPE C; EDETATE DISODIUM; SUNFLOWER OIL; HYPROMELLOSES; MELALEUCA ALTERNIFOLIA LEAF; METHYLISOTHIAZOLINONE; METHYLPARABEN; BLACK OLIVE; HIGH DENSITY POLYETHYLENE; POLYSILICONE-15; POLYSORBATE 20; PROPYLENE GLYCOL; GREEN TEA LEAF; PROPYLPARABEN; SORBITAN MONOOLEATE; SORBITOL; COCOA BUTTER; .ALPHA.-TOCOPHEROL ACETATE; TROLAMINE; WATER

Active ingredients

Avobenzone 2 %, Homosalate 7.5 %, Octisalate 5 %, Octocrylene 2.75 %, and Oxybenzone 2 %

Purpose

Sunscreen

Uses

- helps prevent sunburn
- if used as directed with other sun protection measures (see Directions), decreases the risk of skin cancer and early skin aging caused by the sun

Warnings

OTHER SAFETY INFORMATION

For external use only

Do not use on damaged or broken skin.

When using this product keep out of eyes. Rinse with water to remove.

Stop use and ask a doctor if rash occurs.

Keep out of reach of children. If product is swallowed, get medical help or contact a Poison Control Center right away.

Directions

- apply liberally 15 minutes before sun exposure
- reapply:
  - after 80 minutes of swimming or sweating
  - immediately after towel drying
  - at least every 2 hours
- Sun Protection Measures. Spending time in the sun increases your risk of skin cancer and early skin aging. To decrease this risk, regularly use a sunscreen with a broad spectrum SPF of 15 or higher and other sun protection measures including:
  - limit time in sun, especially from 10 a.m-2 p.m
  - wear long-sleeve shirts, pants, hats, and sunglasses
- Children under 6 months: Ask a doctor

Inactive Ingredients

Acrylates/C10-30 Alkyl Acrylate Crosspolymer, Allantoin, Aloe Barbadensis Leaf Juice, Butylphthalimide, C12-15 Alkyl Benzoate, Carbomer, Disodium EDTA, Fragrance(Parfum), Helianthus Annuus (Sunflower) Seed Oil, Hydroxypropyl Methylcellulose, Isopropylphthalimide, Melaleuca Alternifolia (Tea Tree) leaf Oil, Methylisothiazolinone, Methylparaben, Olea Europaea (Olive) Fruit Oil, Polyethylene, Polysilicone-15, Polysorbate 20, Propylene Glycol, Camellia Sinensis (Green Tea) Leaf Extract, Propylparaben, Sorbitan Oleate, Sorbitol, Theobroma Cacao (Cocoa) Seed Butter, Tocopheryl Acetate, Triethanolamine, Water (Aqua)

Other information

- protect this product from excesive heat and direct sun

Questions or Comments?

Call toll free 1-855-LIV-GOLD (548-4653)

PRINCIPAL DISPLAY PANEL - 237 mL Bottle Label

EXOTIC BLEND

#1 Fragrance

KIDS

30

Lotion

Sunscreen

Moisture Max

BROAD SPECTRUM SPF 30

WATER RESISTANT

(80 MINUTES)

Australian

Gold

237 mL / 8 Fl. Oz